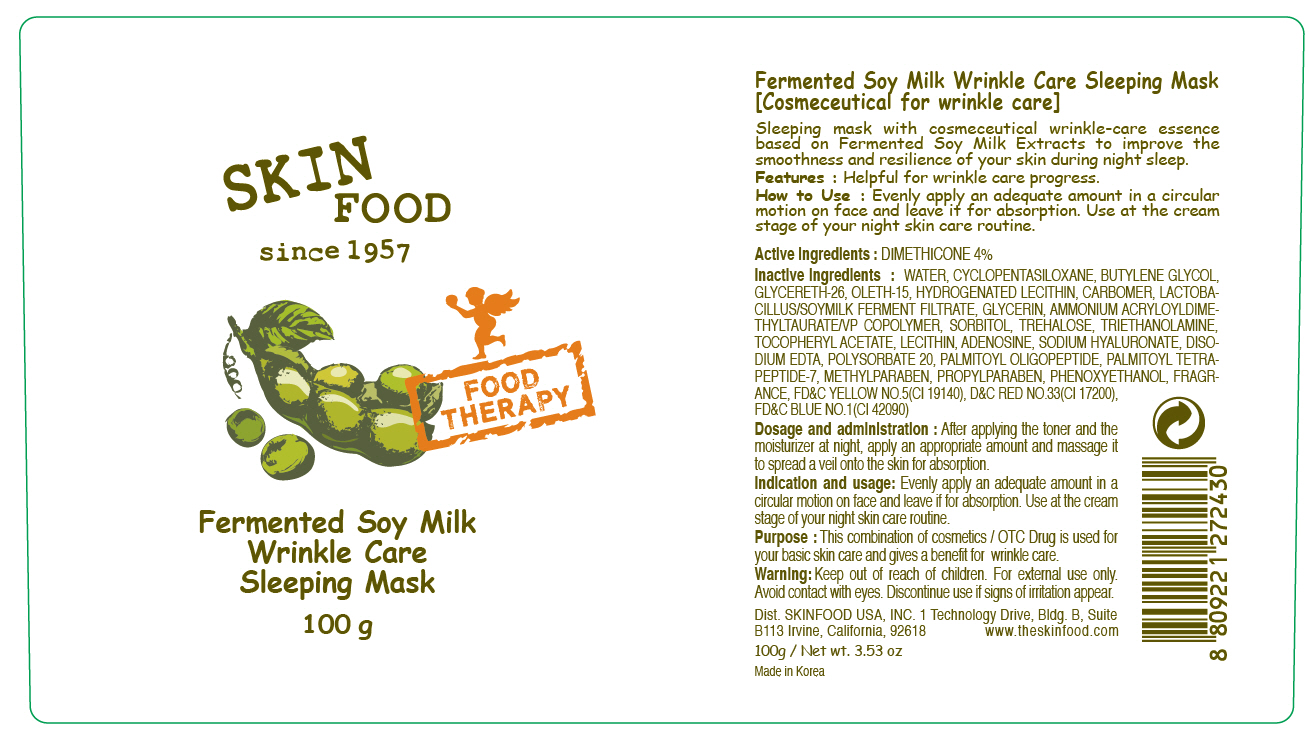 DRUG LABEL: FERMENTED SOY MILK WRINKLE CARE SLEEPING MASK
NDC: 76214-021 | Form: PATCH
Manufacturer: SKINFOOD CO., LTD.
Category: otc | Type: HUMAN OTC DRUG LABEL
Date: 20110921

ACTIVE INGREDIENTS: DIMETHICONE 4 g/100 g
INACTIVE INGREDIENTS: WATER; CYCLOMETHICONE 5; BUTYLENE GLYCOL; GLYCERETH-26; HYDROGENATED SOYBEAN LECITHIN; PHENOXYETHANOL; GLYCERIN; METHYLPARABEN; SORBITOL; TREHALOSE; TROLAMINE; PROPYLPARABEN; LECITHIN, SOYBEAN; ADENOSINE; HYALURONATE SODIUM; EDETATE DISODIUM; POLYSORBATE 20; PALMITOYL OLIGOPEPTIDE; PALMITOYL TETRAPEPTIDE-7

Drug Facts

Active ingredient: DIMETHICONE 4%

Inactive ingredients:
WATER, CYCLOPENTASILOXANE, BUTYLENE GLYCOL, GLYCERETH-26, OLETH-15, HYDROGENATED LECITHIN, CARBOMER, LACTOBACILLUS/SOYMILK FERMENT FILTRATE, GLYCERIN, AMMONIUM ACRYLOYLDIMETHYLTAURATE/VP COPOLYMER, SORBITOL, TREHALOSE, TRIETHANOLAMINE, TOCOPHERYL ACETATE, LECITHIN, ADENOSINE, SODIUM HYALURONATE, DISODIUM EDTA, POLYSORBATE 20, PALMITOYL OLIGOPEPTIDE, PALMITOYL TETRAPEPTIDE-7, METHYLPARABEN, PROPYLPARABEN, PHENOXYETHANOL, FRAGRANCE

PURPOSE

Purpose: This combination of cosmetics / OTC Drug is used for your basic skin care and gives a benefit for wrinkle care.

Warnings:
For external use only.
Avoid contact with eyes.
Discontinue use if signs of irritation appear.

Keep out of reach of children:
Keep out of reach of children.

Indication and usage:
Evenly apply an adequate amount in a circular motion on face and leave if for absorption.
Use at the cream stage of your night skin care routine.

Dosage and administration:
After applying the toner and the moisturizer at night, apply an appropriate amount and massage it to spread a veil onto the skin for absorption.